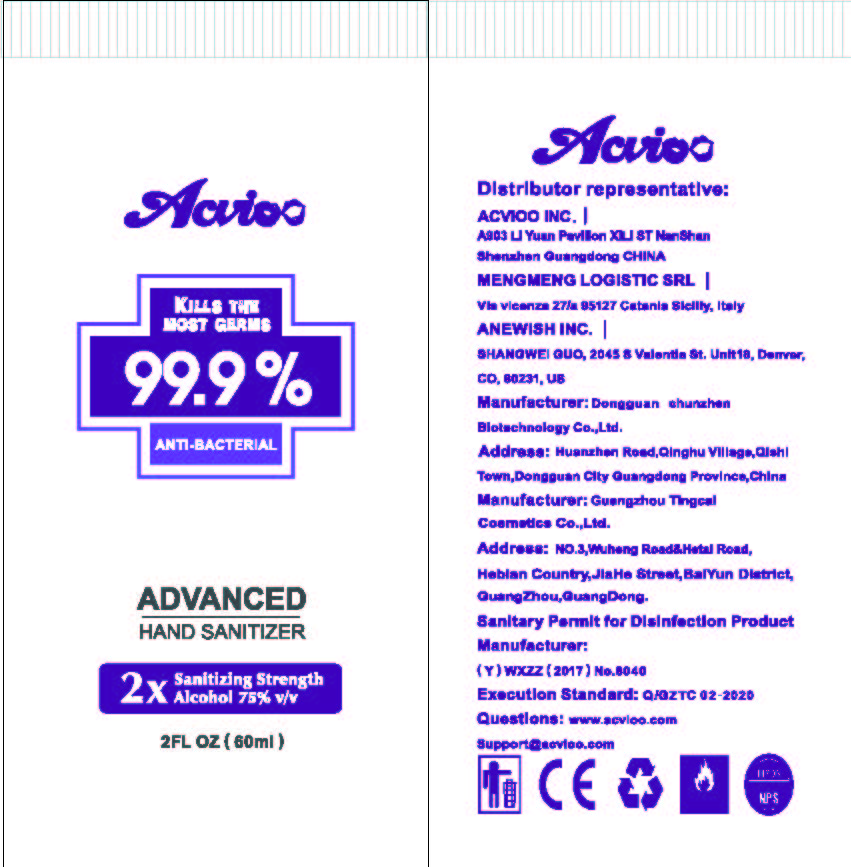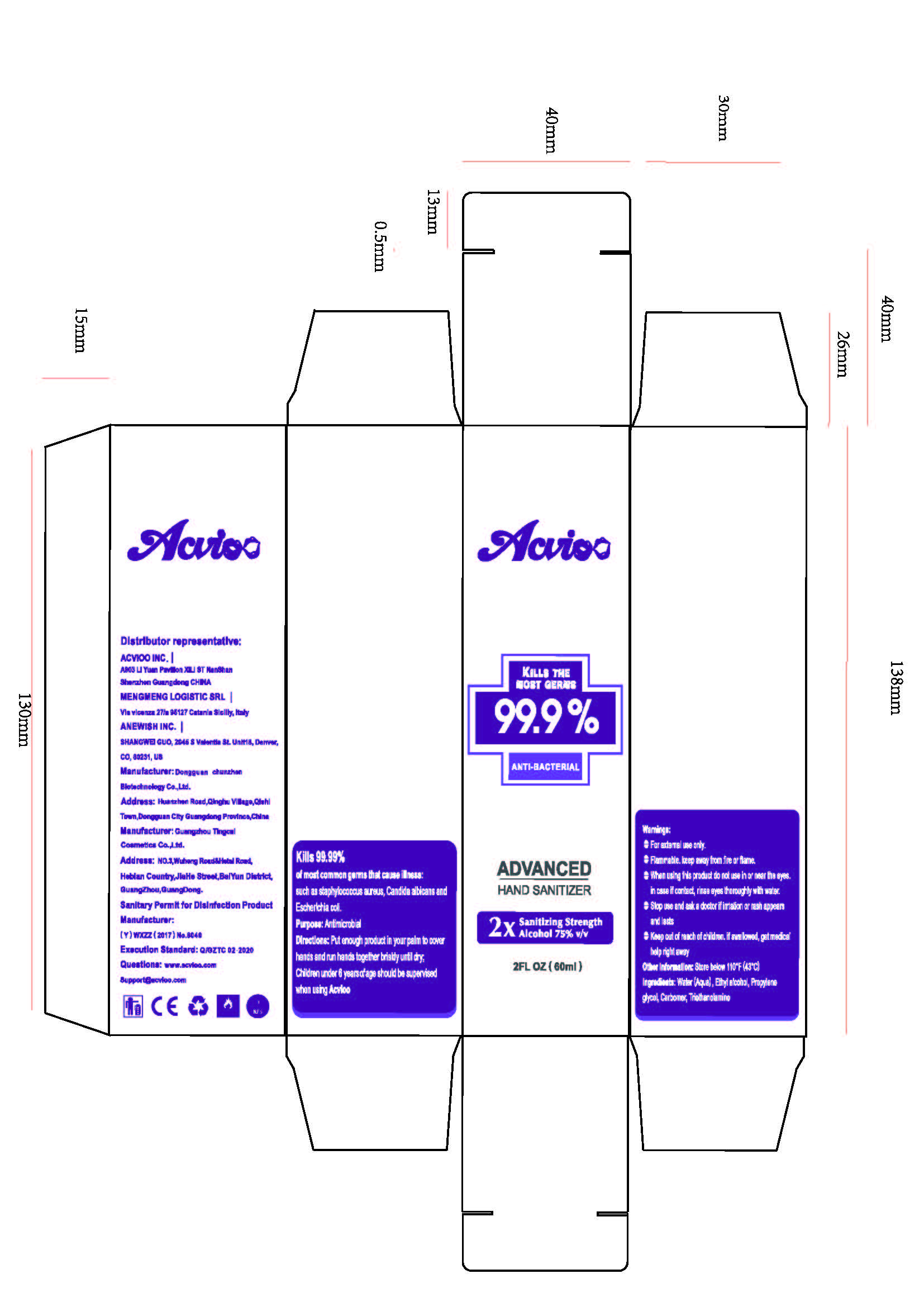 DRUG LABEL: Acvioo Advanced Hand Sanitizer
NDC: 71847-1107 | Form: GEL
Manufacturer: Shenzhen Dikailong Technology Ltd
Category: otc | Type: HUMAN OTC DRUG LABEL
Date: 20200410

ACTIVE INGREDIENTS: ALCOHOL 45 mL/60 mL
INACTIVE INGREDIENTS: SODIUM HYDROXIDE 0.015 mL/60 mL; LEMON 0.03 mL/60 mL; CARBOMER HOMOPOLYMER, UNSPECIFIED TYPE 0.36 mL/60 mL; WATER 13.275 mL/60 mL; GLYCERIN 1.2 mL/60 mL; POLYOXYL 40 HYDROGENATED CASTOR OIL 0.12 mL/60 mL

Acvioo, Hand Sanitizer, Gel, 75% Ethanol, 60mL

Active Ingredient(s)

Ethanol 75% v/v. Purpose: Antiseptic

Purpose

Antiseptic, Hand Sanitizer

Use

Hand Sanitizer to help reduce bacteria that potentially can cause disease. For use when soap and water are not available.

Warnings

Flammable. For external use only. Keep away from heat or flame.

Do not use

- on children less than 2 months of age
- on open skin wounds

When using this product keep out of eyes, ears, and mouth.

In case of contact with eyes, rinse eyes thoroughly with water.

Stop use and ask a doctor if irritation or rash occurs. These may be signs of a serious condition.

Keep out of reach of children. If swallowed, get medical help or contact a Poison Control Center right away.

Directions

- Place enough product on hands to cover all surfaces. Rub hands together until dry.
- Supervise children under 6 years of age when using this product to avoid swallowing.

Other information

- Store between 59-86℉ (15-30℃)
- Avoid freezing and excessive heat above 104℉ (40℃)

Inactive ingredients

Water, Glycerin, Carbomer, PEG-40 Hydrogenated Castor oil, Citrus Limon (Lemon) Fruit Extract, Sodium hydroxide